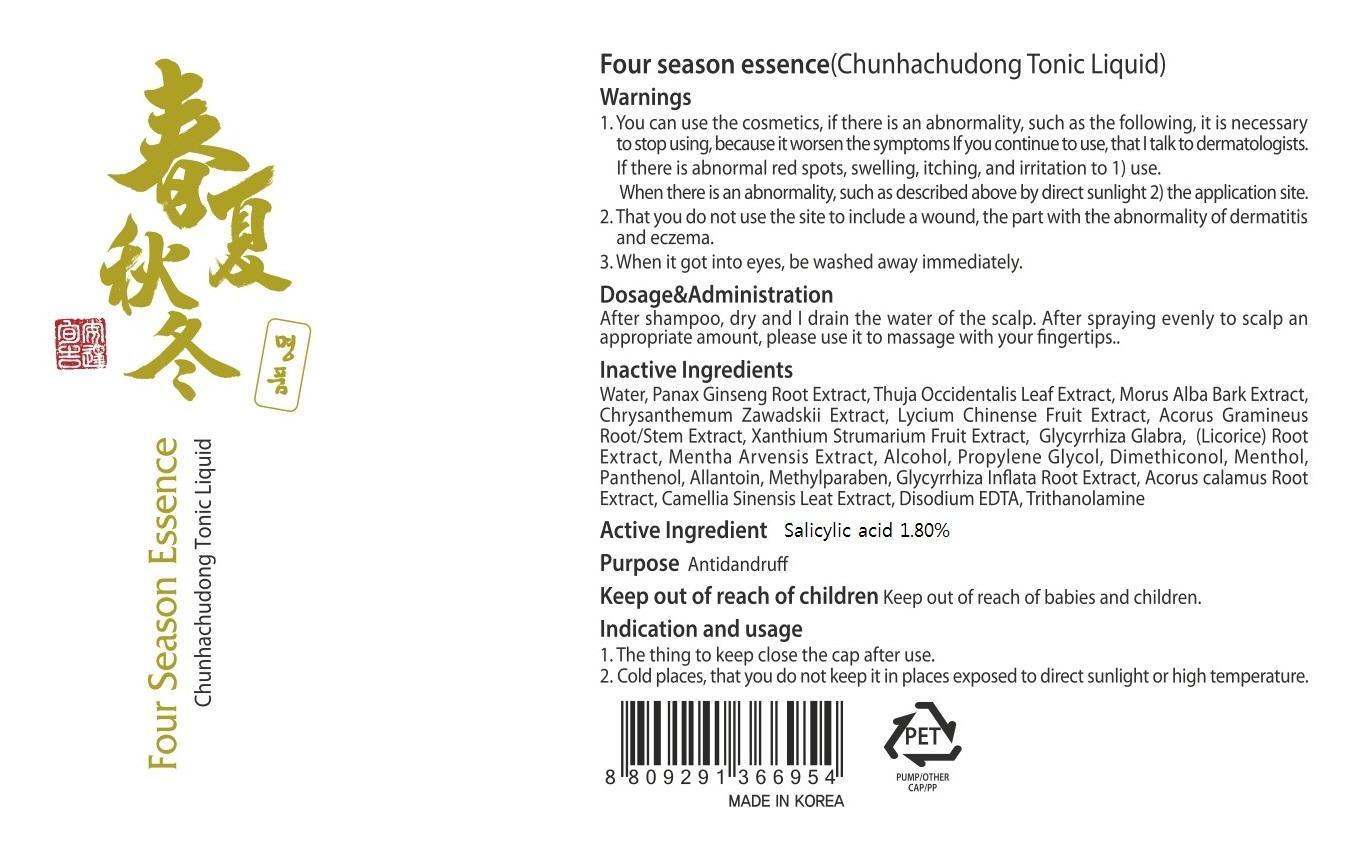 DRUG LABEL: Four Season Essence
NDC: 61616-020 | Form: LIQUID
Manufacturer: OneLineSun Co., Ltd.
Category: otc | Type: HUMAN OTC DRUG LABEL
Date: 20140127

ACTIVE INGREDIENTS: Salicylic acid 2.16 mg/120 mL
INACTIVE INGREDIENTS: Water; PANAX GINSENG ROOT OIL

ACTIVE INGREDIENT

Active Ingredient: Salicylic acid 1.80%

INACTIVE INGREDIENT

Inactive Ingredients:
Water, Panax Ginseng Root Extract, Thuja Occidentalis Leaf Extract, Morus Alba Bark Extract, Chrysanthemum Zawadskii Extract, Lycium Chinense Fruit Extract, Acorus Gramineus Root/Stem Extract, Xanthium Strumarium Fruit Extract, Glycyrrhiza Glabra, (Licorice) Root Extract, Mentha Arvensis Extract, Alcohol, Propylene Glycol, Dimethiconol, Menthol, Panthenol, Allantoin, Methylparaben, Glycyrrhiza Inflata Root Extract, Acorus calamus Root Extract, Camellia Sinensis Leat Extract, Disodium EDTA, Trithanolamine

PURPOSE

Purpose: Antidandruff

WARNINGS

1. You can use the cosmetics, if there is an abnormality, such as the following, it is necessary to stop using, because it worsen the symptoms.
If you continue to use, that I talk to dermatologists.
If there is abnormal red spots, swelling, itching, and irritation to 1) use.
When there is an abnormality, such as described above by direct sunlight 2) the application site.
2. That you do not use the site to include a wound, the part with the abnormality of dermatitis and eczema.
3. When it got into eyes, be washed away immediately.

KEEP OUT OF REACH OF CHILDREN: Keep out of reach of babies and children.

INDICATIONS AND USAGE

1. The thing to keep close the cap after use.
2. Cold places, that you do not keep it in places exposed to direct sunlight or high temperature.

DOSAGE AND ADMINISTRATION

After shampoo, dry and I drain the water of the scalp.
After spraying evenly to scalp an appropriate amount, please use it to massage with your fingertips.